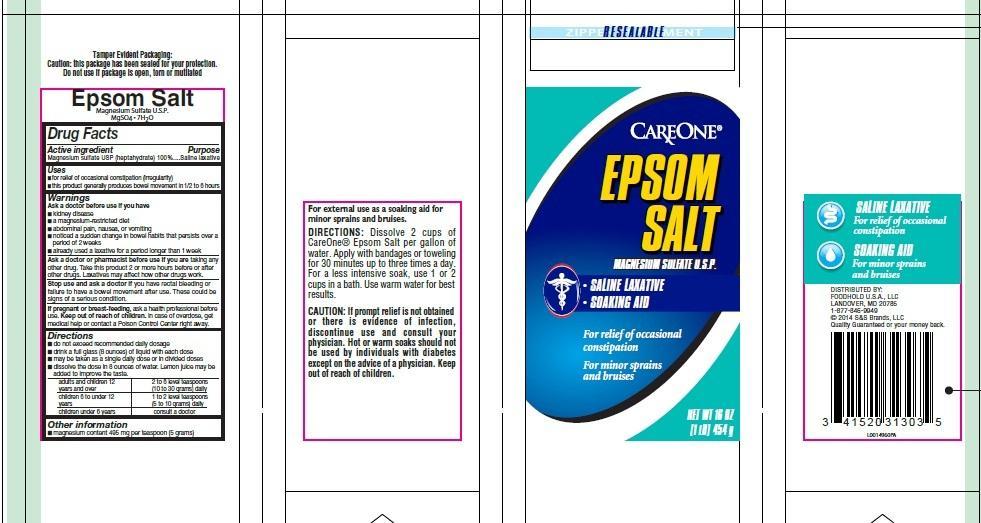 DRUG LABEL: Epsom Salt
NDC: 41520-055 | Form: GRANULE, FOR SOLUTION
Manufacturer: FOODHOLD U.S.A., LLC
Category: otc | Type: HUMAN OTC DRUG LABEL
Date: 20250224

ACTIVE INGREDIENTS: MAGNESIUM SULFATE HEPTAHYDRATE 1 g/1 g

Care One 602
Epsom Salt

TEP

Tamper Evident Packaging:

Caution: this package has been sealed for your protection.

Do not use if package is open, torn or mutilated

Claims

Epsom Salt

Magnesium Sulfate U.S.P.

MgSO4 - 7H2O

Active ingredient

Magnesium sulfate USP (heptahydrate) 100%

Purpose

Saline Laxative

External use soaking aid

Uses

- for relief of occasional constipation (irregularity)
- this product generally produces bowel movement in 1/2 to 6 hours

For external use as a soaking aid for minor sprains and bruises

Warnings

CAUTION: If prompt relief is not obtained or there is evidence of infection, discontinue use and consult your physician.

Hot or warms soaks should not be used by individuals with diabetes except on the advice of a physican

Ask a doctor before use if you have

- kidney disease
- a magnesium-restricted diet
- abdominal pain, nausea, or vomiting
- noticed a sudden change in bowel habits that persists over a period of 2 weeks
- already used a laxative for a period longer than 1 week

Ask a doctor or pharmacist before use if you are

taking any other drug. Take this product 2 or more hours before or after other drugs. Laxatives may affect how other drugs work.

Stop use and ask a doctor if

you have rectal bleeding or failure to have a bowel movement after use. These could be signs of a serious condition.

If pregnant or breast-feeding

ask a health professional before use.

Keep out of reach of children

In case of overdose, get medical help or contact a Poison Control Center right away.

Directions

- do not exceed recommended daily dosage
- drink a full glass (8 ounces) of liquid with each dose
- may be taken as a single daily dose or in divided doses
- dissolve the dose in 8 ounces of water. Lemon juice may be added to improve the taste

adults and children 12 years and over - 2 to 6 level teaspoons (10 to 30 grams) daily

children 6 to under 12 years - 1 to 2 level teaspoons (5 to 10 grams) daily

children under 6 years - consult a doctor

Directions for Soaking:

Dissolve 2 cups of CareOne Epsom Salt per fallon of water. Apply with bandages or toweling for 30 minutes up to three times a day. For less intensive soak, use 1 or 2 cups in a bath. Use warm water for best results

Other information

- magnesium content 495 mg per teaspoon (5 grams)

INACTIVE INGREDIENT SECTION

None

Adverse Reactions

DISTRIBUTED BY:

FOODHOLD U.S.A., LLC

LANDOVER, MD 20785

Quality Guaranteed or your money back.

principal display panel

CAREONE

EPSOM

SALKT

MAGNESIUM SULFATE U.S.P.

- SALINE LAXATIVE
- SOAKING AID

For relief of occasional constipation

For minor sprains and bruises

NET WT 16 OZ

(1 LB) 454 g